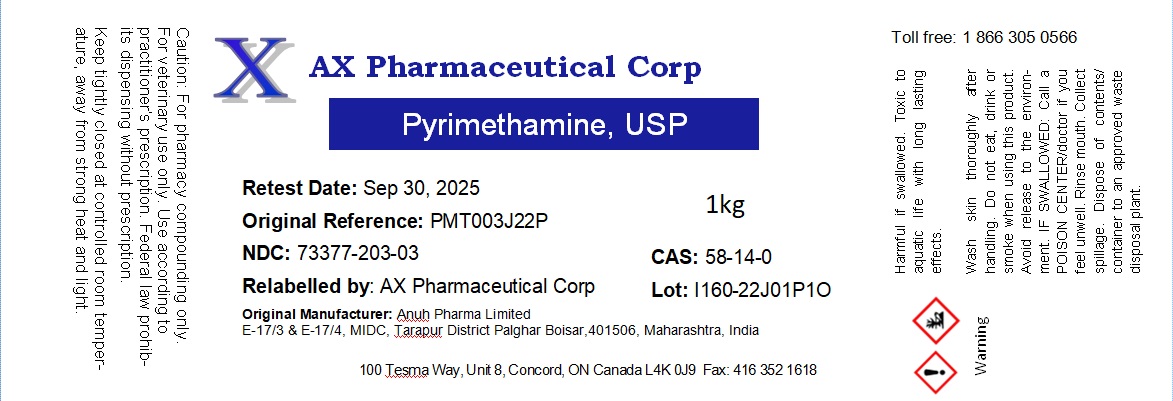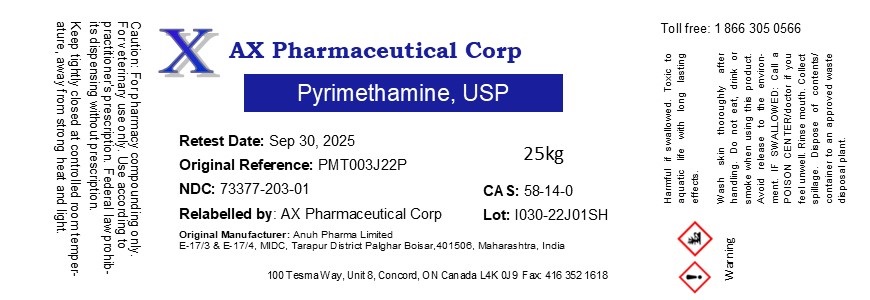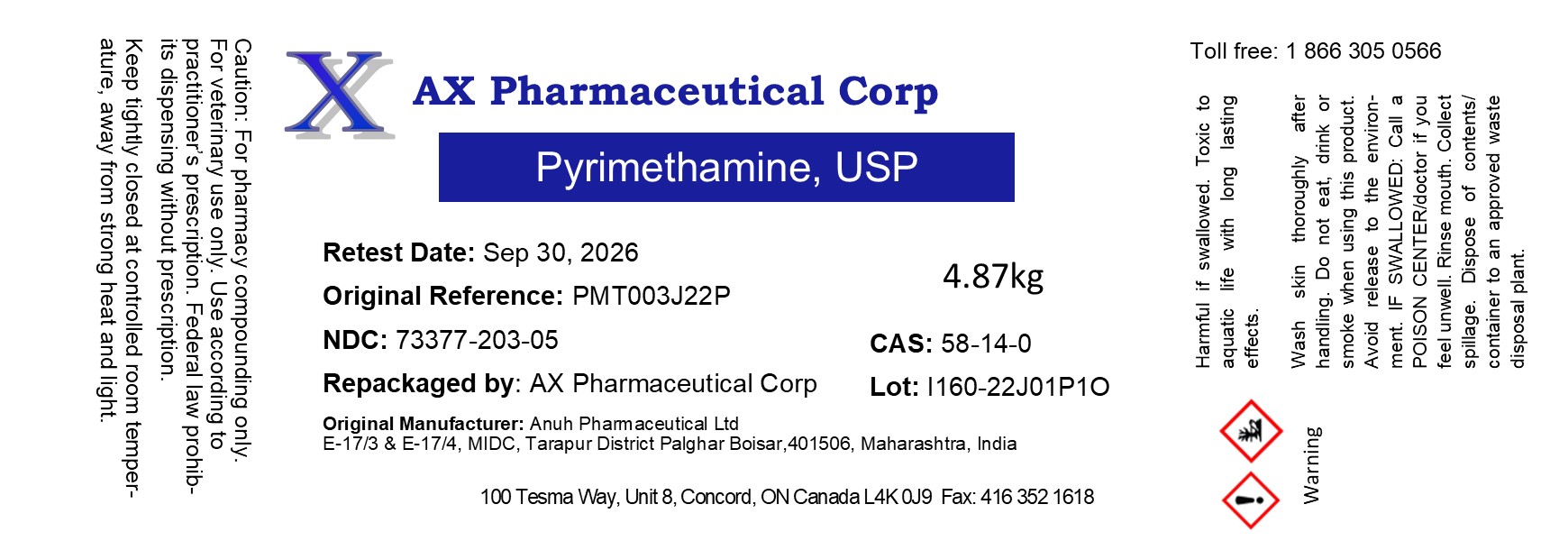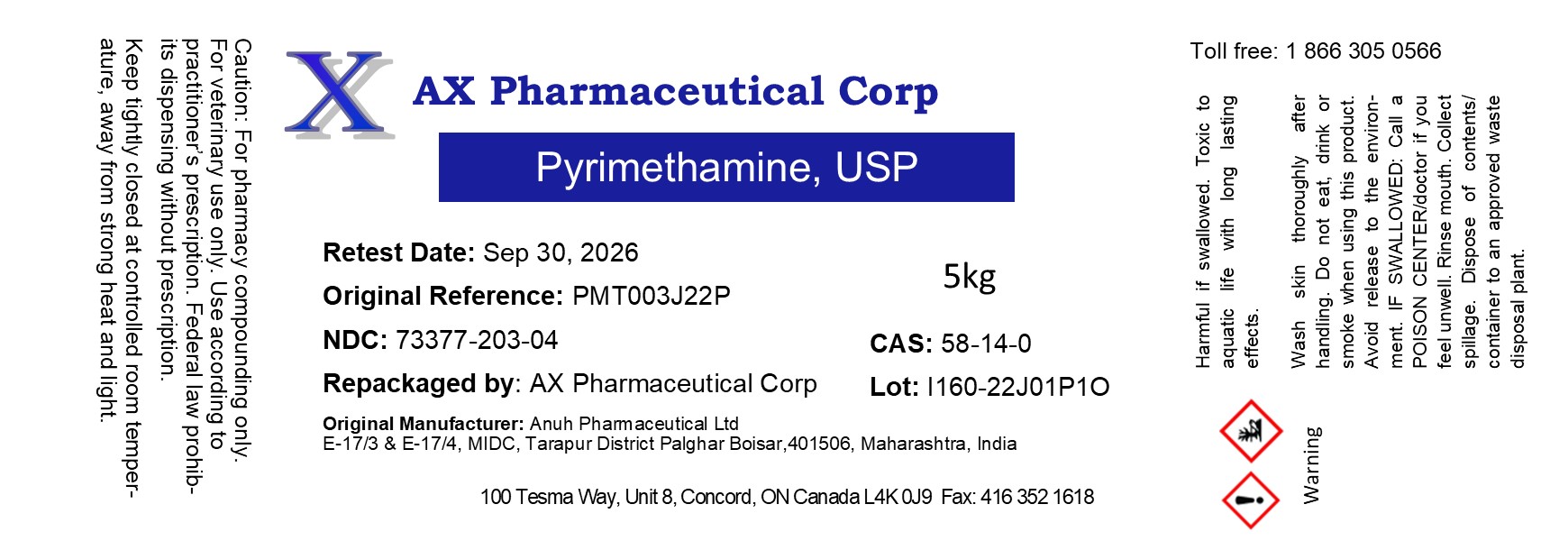 DRUG LABEL: Pyrimethamine
NDC: 73377-203 | Form: POWDER
Manufacturer: AX Pharmaceutical Corp
Category: other | Type: BULK INGREDIENT - ANIMAL DRUG
Date: 20241029

ACTIVE INGREDIENTS: PYRIMETHAMINE 1 kg/1 kg

Pyrimethamine